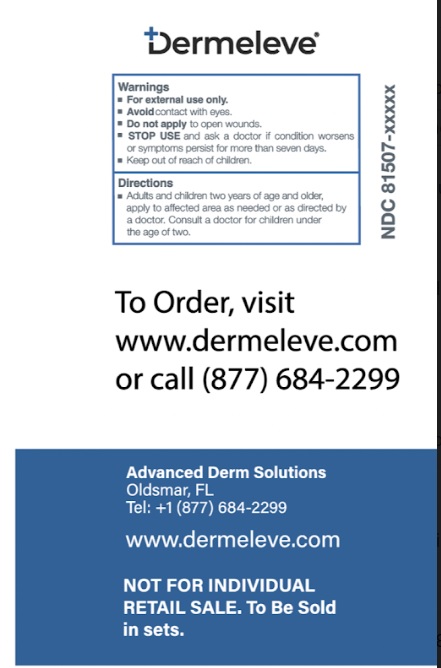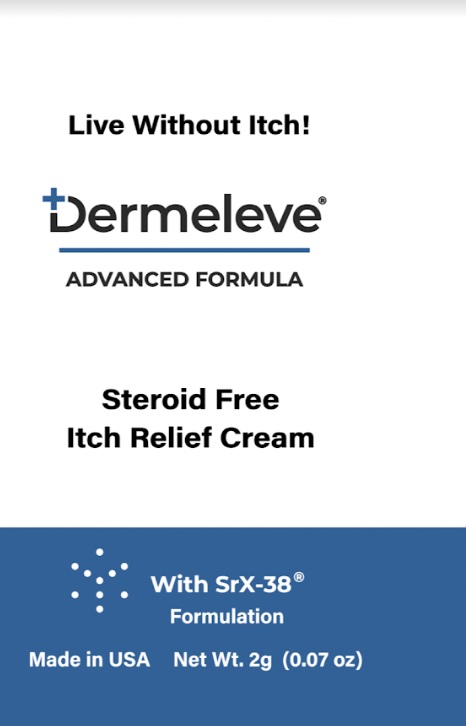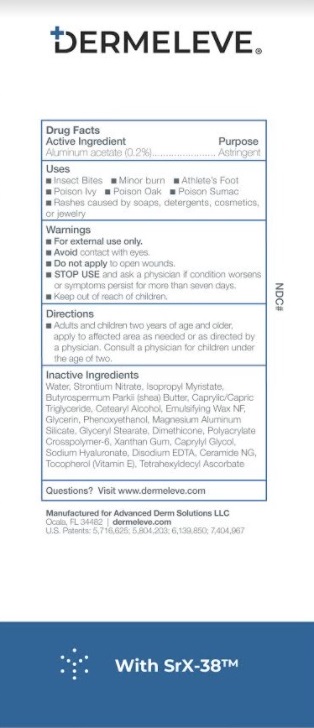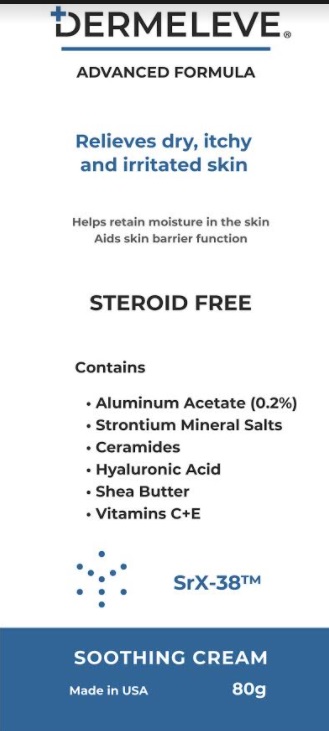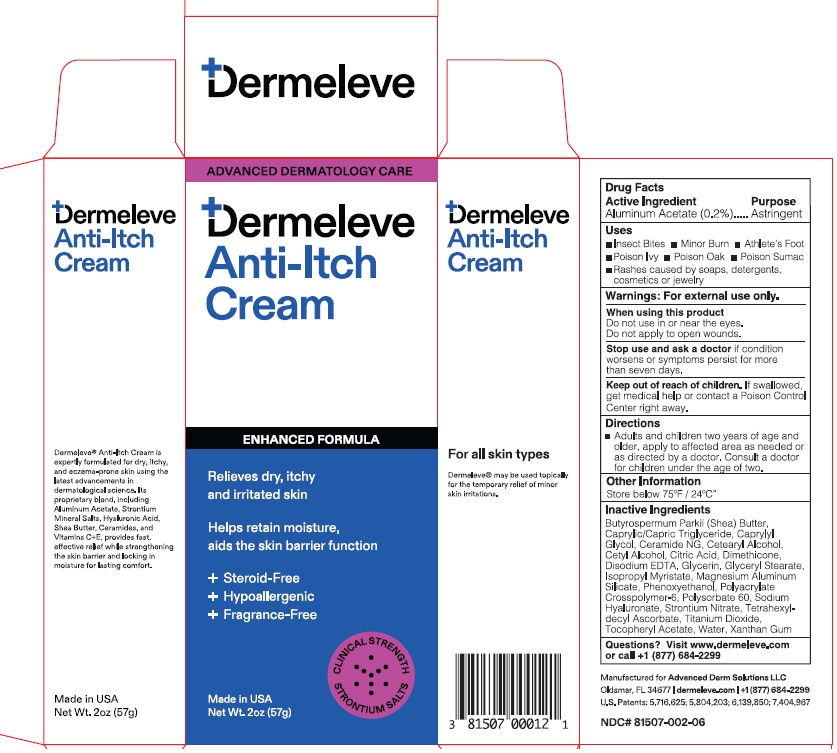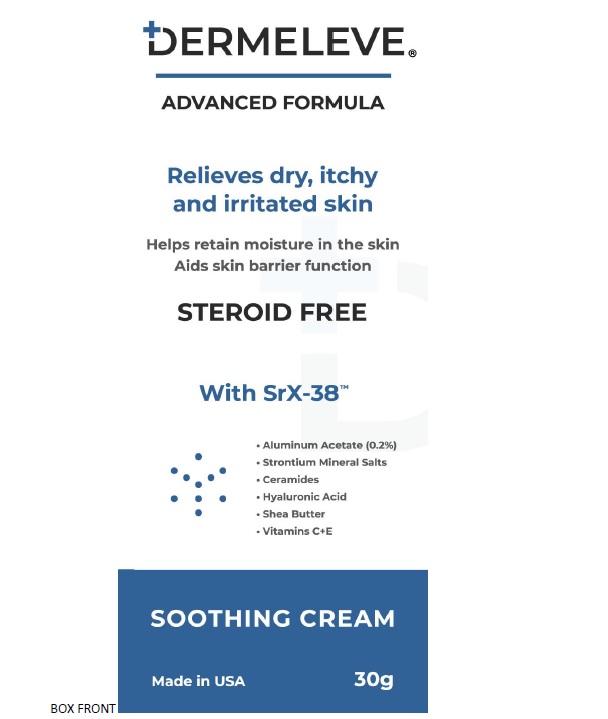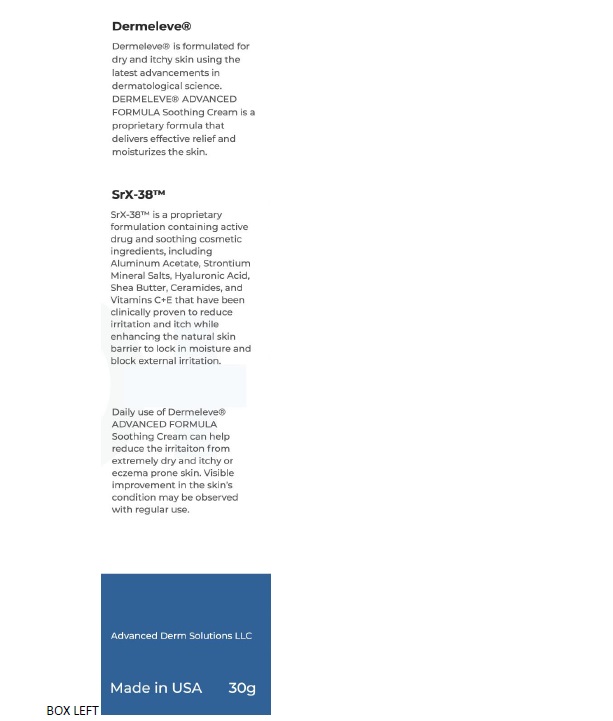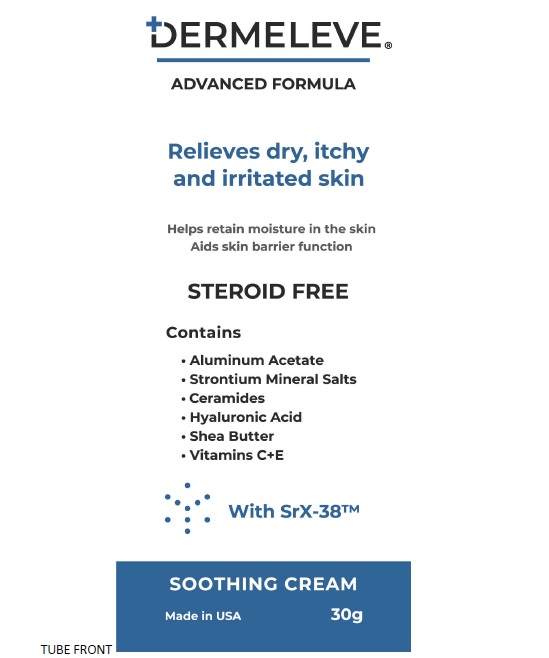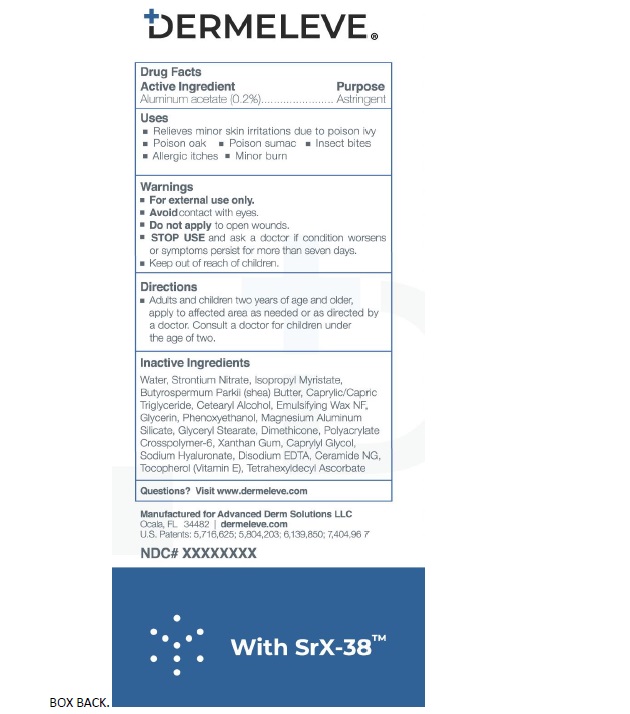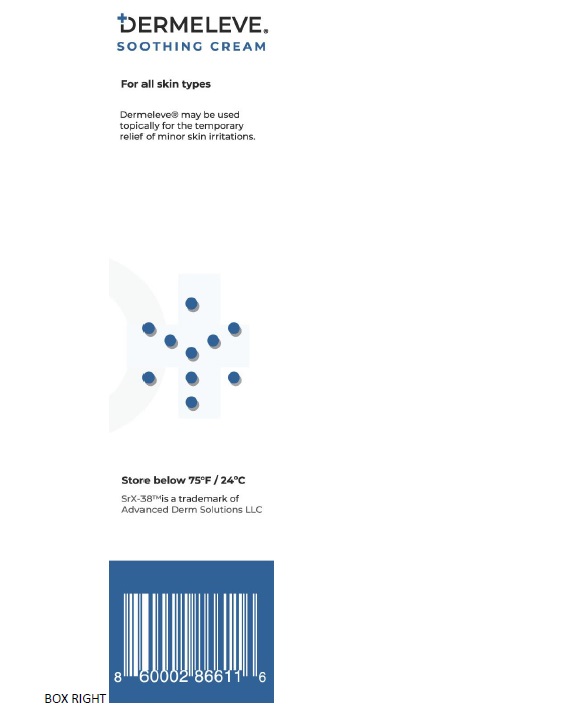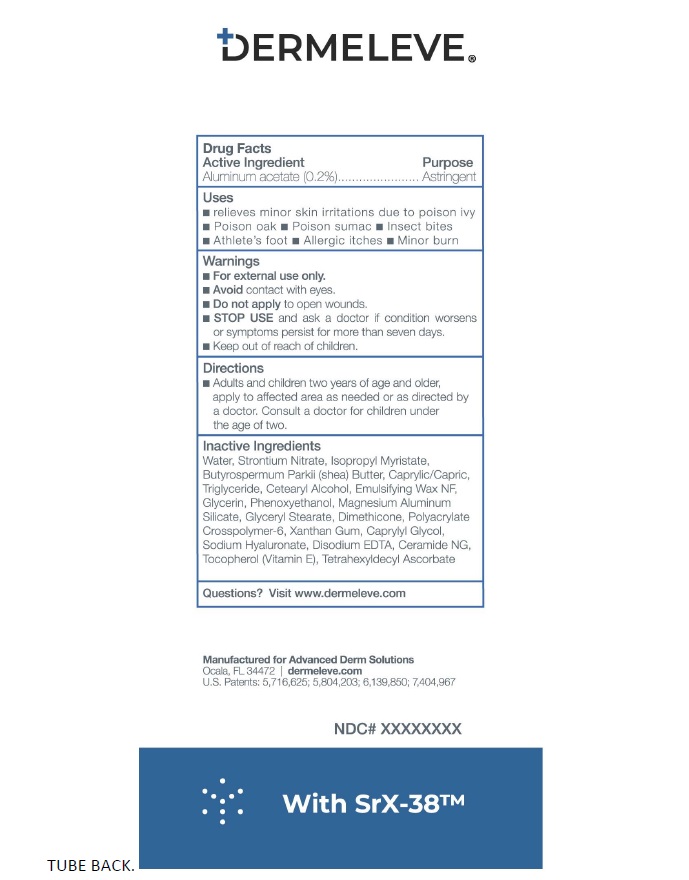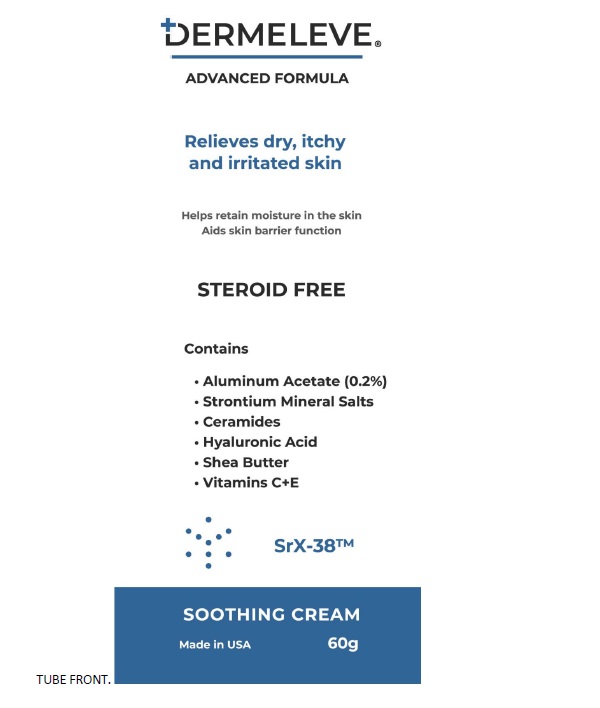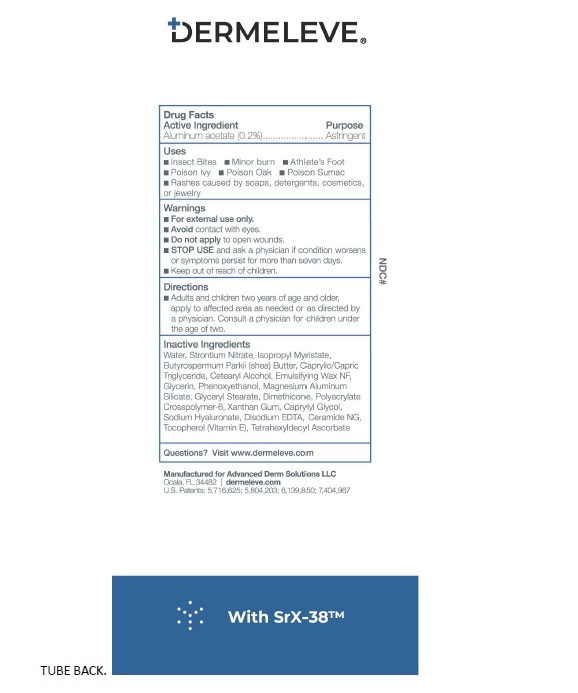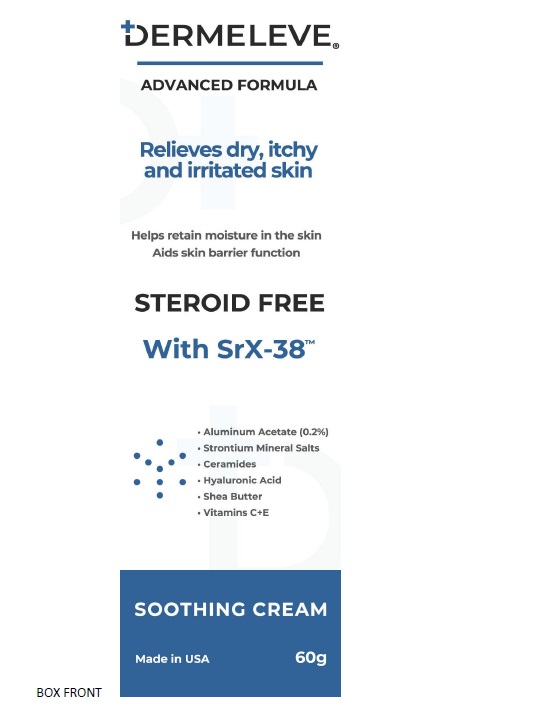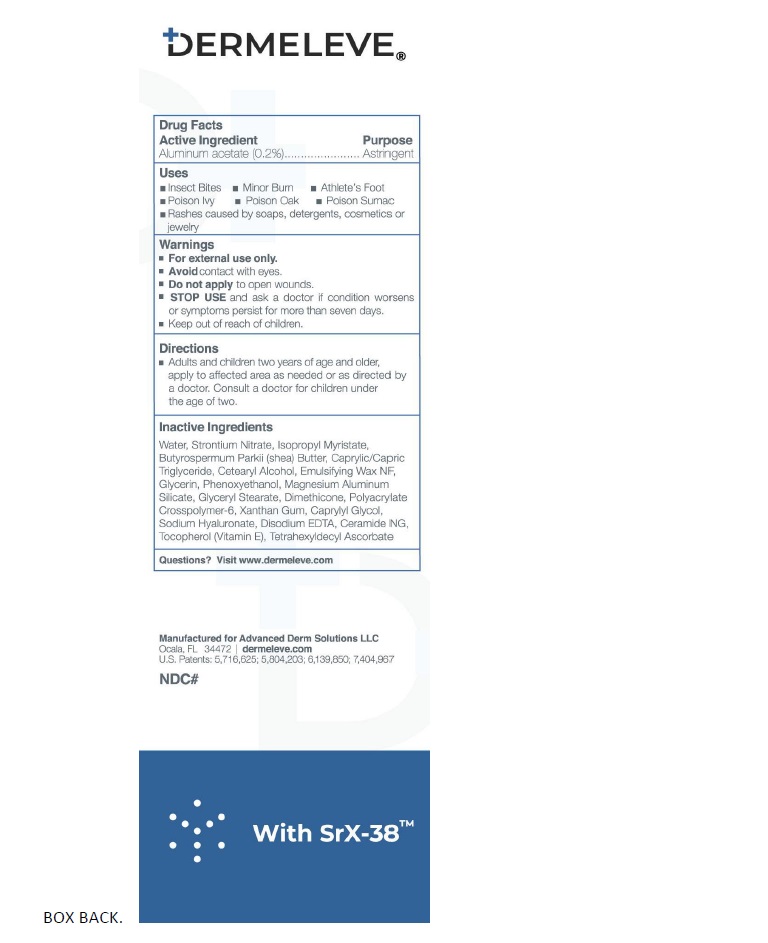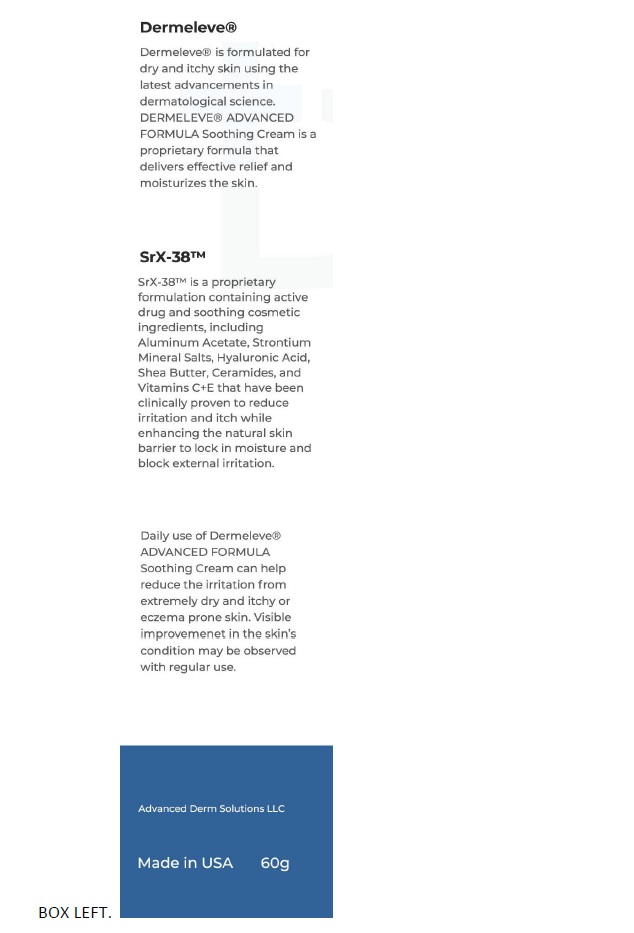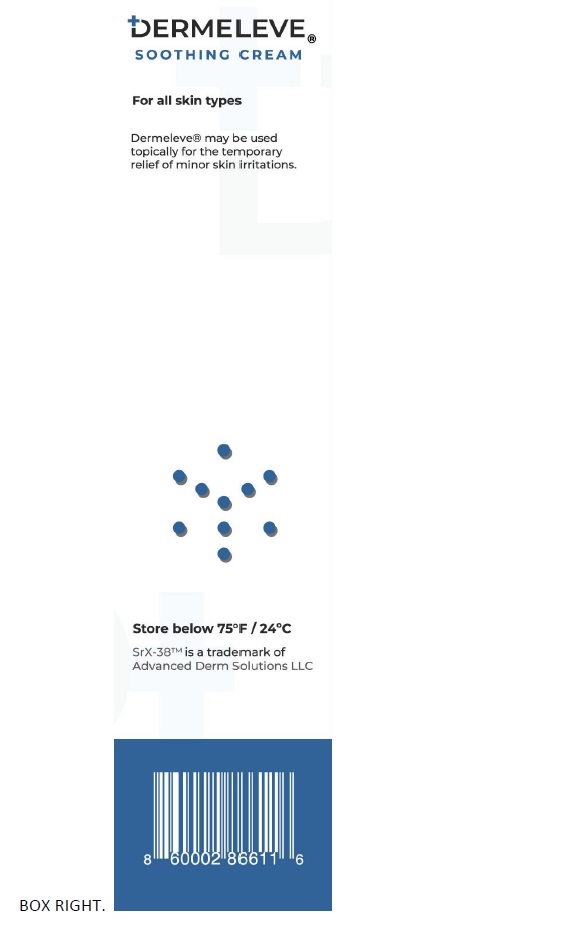 DRUG LABEL: Dermeleve
NDC: 81507-002 | Form: CREAM
Manufacturer: Advanced Derm Solutions LLC
Category: otc | Type: HUMAN OTC DRUG LABEL
Date: 20250529

ACTIVE INGREDIENTS: ALUMINUM ACETATE 0.2 g/100 g
INACTIVE INGREDIENTS: SHEA BUTTER; TRICAPRIN; CAPRYLYL GLYCOL; CERAMIDE NG; CETOSTEARYL ALCOHOL; CETYL ALCOHOL; CITRIC ACID MONOHYDRATE; DIMETHICONE, UNSPECIFIED; EDETATE DISODIUM; GLYCERIN; GLYCERYL STEARATE/PEG-100 STEARATE; ISOPROPYL MYRISTATE; MAGNESIUM ALUMINUM SILICATE; PHENOXYETHANOL; AMMONIUM ACRYLOYLDIMETHYLTAURATE, DIMETHYLACRYLAMIDE, LAURYL METHACRYLATE AND LAURETH-4 METHACRYLATE COPOLYMER, TRIMETHYLOLPROPANE TRIACRYLATE CROSSLINKED (45000 MPA.S); POLYSORBATE 60; HYALURONATE SODIUM; STRONTIUM NITRATE; TETRAHEXYLDECYL ASCORBATE; TITANIUM DIOXIDE; .ALPHA.-TOCOPHEROL ACETATE; WATER; XANTHAN GUM

Active Ingredient

Aluminum acetate (0.2%)

Purpose

Astringent

Uses

• Insects Bites
• Minor Burn
• Athlete's foot
• Poison lvy
• Poison oak
• Poison sumac
• Rashes cause by soaps, detergents, cosmetic or jewelry

Warnings

■ For external use only.
■ Avoidcontact with eyes.
■ Do not applyto open wounds.
■ STOP USEand ask a doctor if condition worsens
or symptoms persist for more than seven days.

■ Keep out of reach of children.

Directions

Adults and children two years of age and older,
apply to affected area as needed or as directed by a doctor. Consult a doctor for children under the age of two.

Inactive ingredients

Butyrospermum Parkii (Shea) Butter, Caprylic/Capric Triglyceride, Caprylyl Glycol, Ceramide NG, Cetearyl Alcohol, Cetyl Alcohol, Citric Acid

Dimethicone, Disodium EDTA, Glycerin, Glyceryl Stearate, Isopropyl Myristate, Magnesium Aluminum Silicate, Phenoxyethanol, Polyacrylate

Crosspolymer-6, Polysorbate 60, Sodium Hyaluronate, Strontium Nitrate, Tetrahexyldecyl Ascorbate, Titanium Dioxide, Tocopheryl Acetate

Water, Xanthan Gum

Questions ? Visit www.dermeleve.com

Manufactured for Advanced Derm Solutions LLC
Ocala, FL 34482 | dermeleve.com
U.S. Patents: 5,716,625; 5,804,203; 6,139,850; 7,404,967